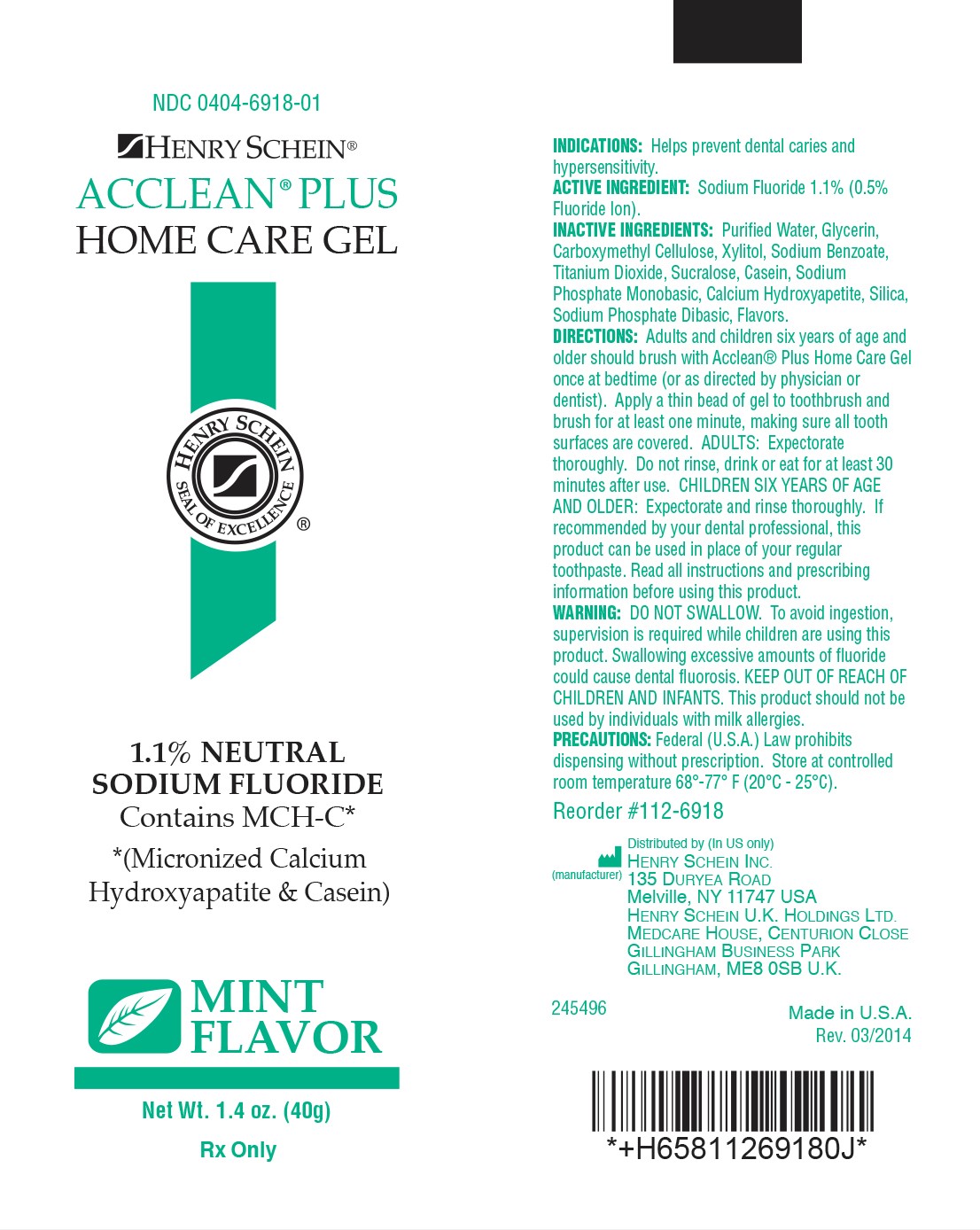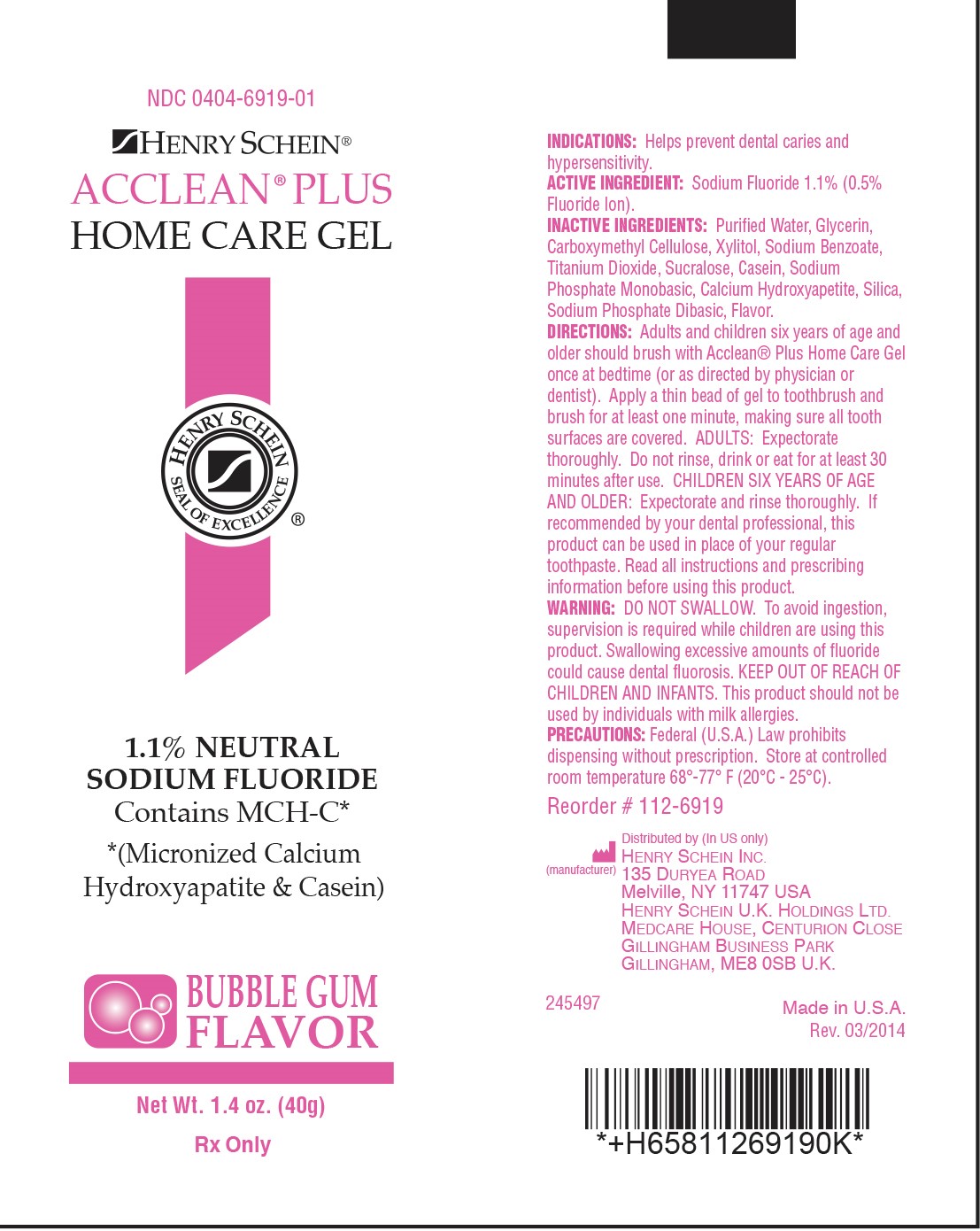 DRUG LABEL: Acclean Plus 
NDC: 0404-6918 | Form: GEL, DENTIFRICE
Manufacturer: Henry Schein, Inc.
Category: prescription | Type: HUMAN PRESCRIPTION DRUG LABEL
Date: 20181103

ACTIVE INGREDIENTS: SODIUM FLUORIDE 11 mg/1 g
INACTIVE INGREDIENTS: WATER; GLYCERIN; XYLITOL; Carboxymethylcellulose; Sodium Benzoate; Titanium Dioxide; Sucralose; Casein; Sodium Phosphate, Monobasic; Tribasic Calcium Phosphate; Silicon Dioxide; Sodium Phosphate, Dibasic

Inactive Ingredients

Purified Water, Glycerin, Carboxymethyl Cellulose, Xylitol, Sodium Benzoate, Titanium Dioxide, Sucralose, Casein, Sodium Phosphate Monobasic, Calcium Hydroxyapetite, Silica, Sodium Phosphate Dibasic, Flavor.

Active Ingredient

Sodium Fluoride 1.1%

(0.5% Fluoride Ion)

Indications

Helps prevent dental caries and hypersensitivity.

Directions

Adults and children six years of age and older should brush with Acclean® Plus Home Care Gel once at bedtime (or as directed by physician or dentist). Apply a thin bead of gel to toothbrush and brush for at least one minute, making sure all tooth surfaces are covered. ADULTS: Expectorate thoroughly. Do not rinse, drink or eat for at least 30 minutes after use. CHILDREN SIX YEARS OF AGE AND OLDER: Expectorate and rinse thoroughly. If recommended by your dental professional, this product can be used in place of your regular toothpaste. Read all instructions and prescribing information before using this product.

Warning

DO NOT SWALLOW. To avoid ingestion, supervision is required while children are using this product. Swallowing excessive amounts of fluoride could cause dental fluorosis. KEEP OUT OF REACH OF CHILDREN AND INFANTS. This product should not be used by individuals with milk allergies.

Precautions

Federal (U.S.A.) Law prohibits dispensing without prescription. Store at controlled room temperature 68º - 77º F (20ºC - 25ºC).
Reorder # 112-6918
Reorder # 112-6919
Distributed by (In US Only) HENRY SCHEIN INC.
135 DURYEA ROAD
Melville, NY 11747 USA

Package Label

NDC 0404-6918-01
HENRY SCHEIN®
ACCLEAN® PLUS
HOME CARE GEL
HENRY SCHEIN SEAL OF EXCELLENCE®
1.1% NEUTRAL SODIUM FLUORIDE
Contains MCH-C*
*(Micronized Calcium Hydroxyapatite & Casein)
MINT FLAVOR
Net Wt. 1.4 oz. (40g)
Rx Only

NDC 0404-6919-01
HENRY SCHEIN®
ACCLEAN® PLUS
HOME CARE GEL
HENRY SCHEIN SEAL OF EXCELLENCE®
1.1% NEUTRAL SODIUM FLUORIDE
Contains MCH-C*
*(Micronized Calcium Hydroxyapatite & Casein)
BUBBLE GUM FLAVOR
Net Wt. 1.4 oz. (40g)
Rx Only